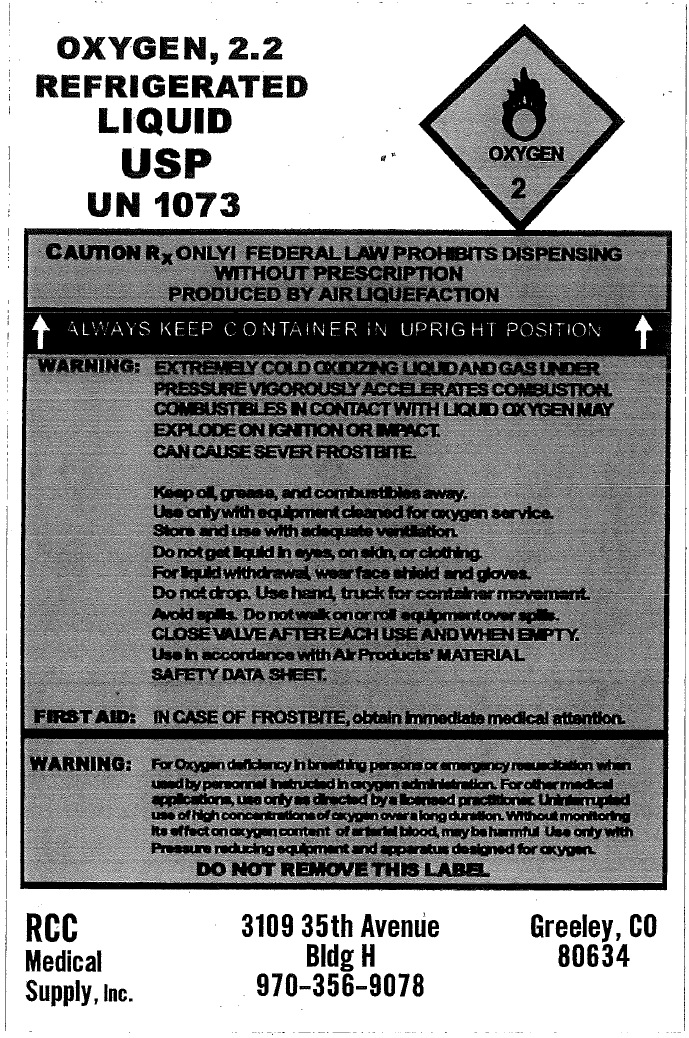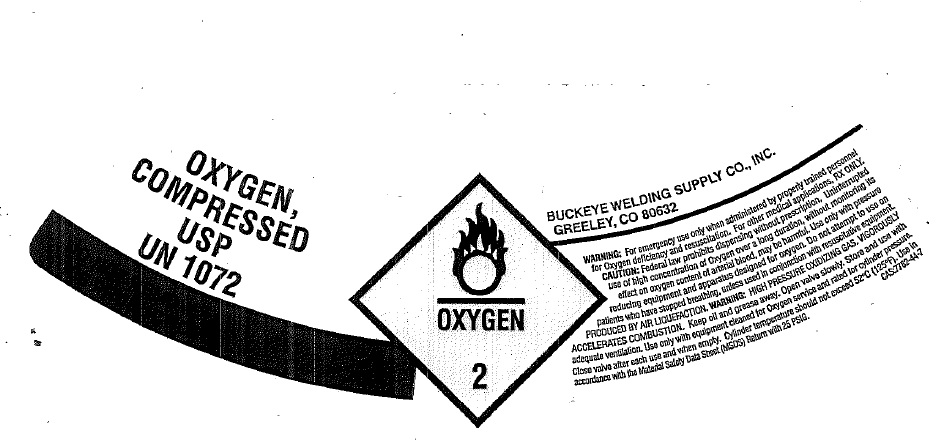 DRUG LABEL: Oxygen Compressed UN 1072 Refrigerated UN 1073
NDC: 61393-0003 | Form: GAS
Manufacturer: Superior Medical Equipment Company, LLC
Category: prescription | Type: HUMAN PRESCRIPTION DRUG LABEL
Date: 20241127

ACTIVE INGREDIENTS: OXYGEN 1 L/1 L

Oxygen Compressed USP UN 1072 Refrigerated Liquid USP UN 1073